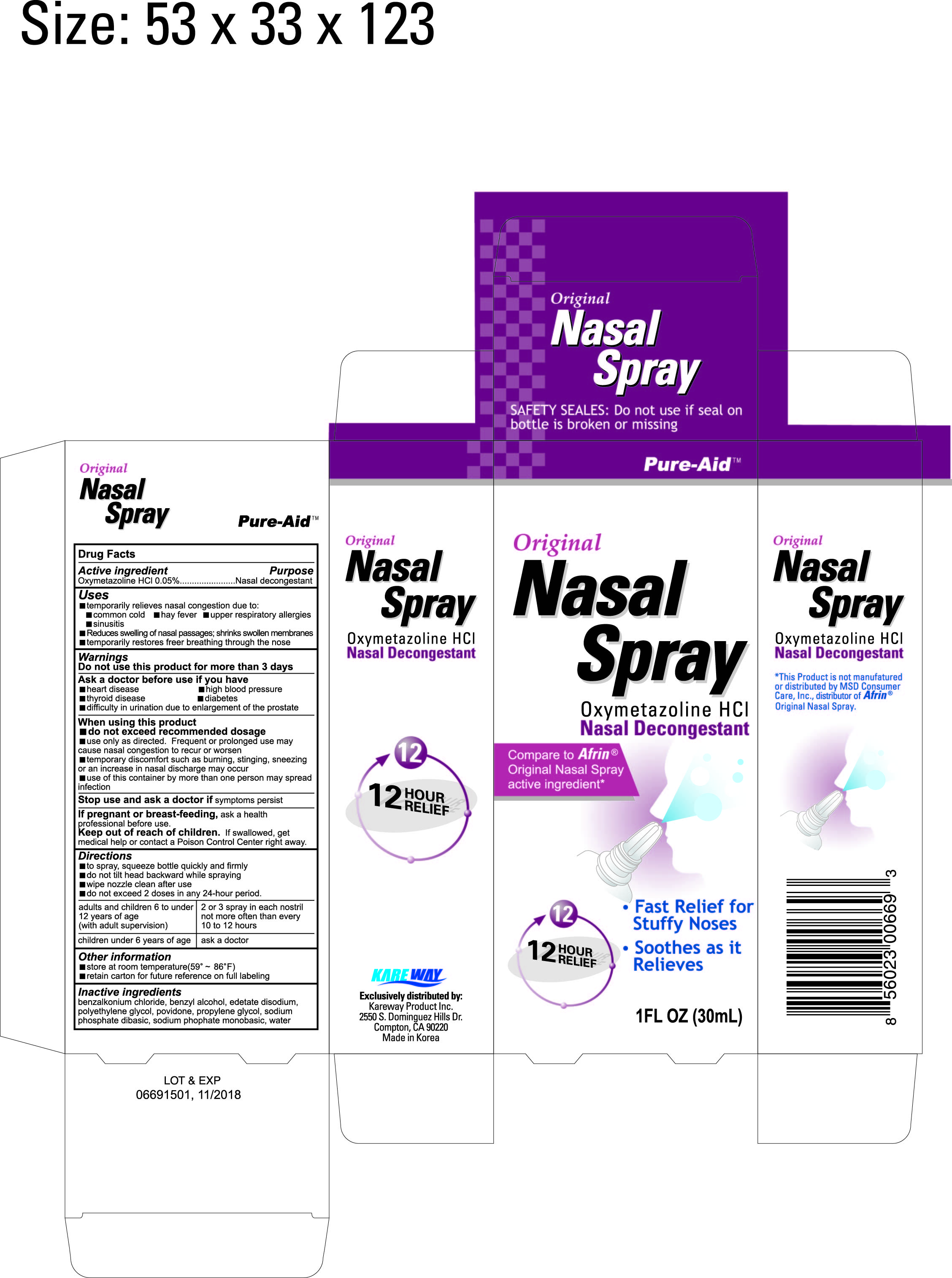 DRUG LABEL: Nasal Decongestant
NDC: 67510-0669 | Form: SPRAY
Manufacturer: Kareway Product, Inc.
Category: otc | Type: HUMAN OTC DRUG LABEL
Date: 20151123

ACTIVE INGREDIENTS: OXYMETAZOLINE HYDROCHLORIDE 0.05 g/100 mL
INACTIVE INGREDIENTS: BENZALKONIUM CHLORIDE; BENZYL ALCOHOL; EDETATE DISODIUM; POLYETHYLENE GLYCOLS; POVIDONE; PROPYLENE GLYCOL; SODIUM PHOSPHATE, DIBASIC; SODIUM PHOSPHATE, MONOBASIC; WATER

Drug Facts

Active ingredient

Oxymetazoline HCl 0.05%

Purpose

Nasal decongestant

Uses

- temporarily relieves nasal congestion due to:

- common cold
- hay fever
- upper respiratory allergies
- sinusitis

- reduces swelling of nasal passages; shrinks swollen membranes
- temporarily restores freer breathing through the nose

Warnings

Do not use this product for more than 3 days

Ask a doctor before use if you have

- heart disease
- high blood pressure
- thyroid disease
- diabetes
- difficulty in urination due to enlargement of the prostate

When using this product

- do not exceed recommended dosage
- use only as directed. frequent of prolonged use may cause nasal congestion to recur or worsen
- temporary discomfort such as burning, stinging, or an increase in nasal discharge may occur
- use of this container by more than one person may spread infection

Stop use and ask a doctor if

symptoms persist

If pregnant or breast-feeding,

ask a health professional before use.

Keep out of reach of children.

If swallowed, get medical help or contact a Poison Control Center right away.

Directions

- To spray, squeeze bottle qiuckly and firmly
- Do not tilt head backward while spraying
- Wipe nozzle clean after use
- Do not exceed 2 doses in any 24 hour period
- adults and children 6 to under 12 years of age (with adult supervision): 2 or 3 sprays in each nostril not more often than every 10 to 12 hours
- chlidren under 6 years of age: ask a doctor

Other information

- store at room temperature 15° - 30°C (59°-86°F)

- retain carton for future reference on full labeling

Inactive ingredients

benzalkonium chloride, benzyl alcohol, edetate disodium, polyethylene glycol, povidone, propylene glycol, sodium phosphate dibasic, sodium phosphate monobasic, water